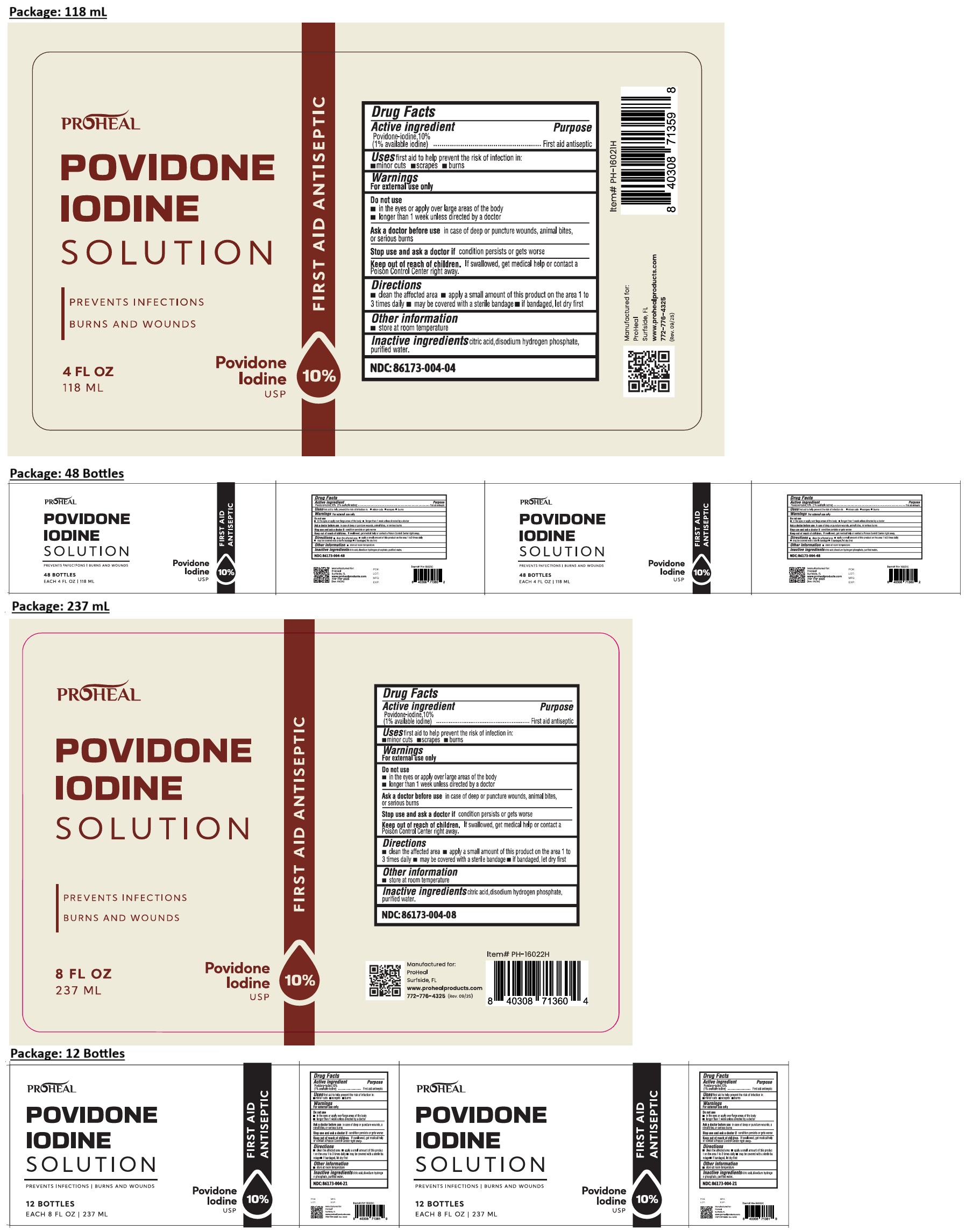 DRUG LABEL: PROHEAL POVIDONE IODINE
NDC: 86173-004 | Form: SOLUTION
Manufacturer: Click Industries LLC
Category: otc | Type: HUMAN OTC DRUG LABEL
Date: 20251209

ACTIVE INGREDIENTS: POVIDONE-IODINE 1 g/100 mL
INACTIVE INGREDIENTS: CITRIC ACID MONOHYDRATE; SODIUM PHOSPHATE, DIBASIC, ANHYDROUS; WATER

PROHEAL POVIDONE IODINE SOLUTION

Active ingredient

Povidone-iodine, 10% (1% available iodine)

Purpose

First aid antiseptic

Uses

first aid to help prevent the risk of infection in: • minor cuts • scrapes • burns

Warnings

For external use only

Do not use
• in the eyes or apply over large areas of the body • longer than 1 week unless directed by a doctor

Ask a doctor before use in case of deep or puncture wounds, animal bites, or serious burns

Stop use and ask a doctor if condition persists or gets worse

Keep out of reach of children. If swallowed, get medical help or contact a Poison Control Center right away.

Directions

• clean the affected area • apply a small amount of this product on the area 1 to 3 times daily • may be covered with a sterile bandage • if bandaged, let dry first

Other information

• store at room temperature

Inactive ingredients

citric acid, disodium hydrogen phosphate, purified water.

PREVENTS INFECTIONS ǀ BURNS AND WOUNDS

FIRST AID ANTISEPTIC

Manufactured for:
ProHeal
Surfside, FL
www.prohealproducts.com
772-776-4325